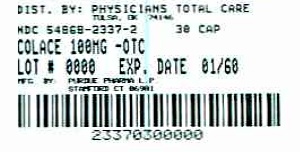 DRUG LABEL: Colace
NDC: 54868-2337 | Form: CAPSULE
Manufacturer: Physicians Total Care, Inc.
Category: otc | Type: HUMAN OTC DRUG LABEL
Date: 20100329

ACTIVE INGREDIENTS: docusate sodium 100 mg/1 1
INACTIVE INGREDIENTS: D&C RED NO. 33; FD&C RED NO. 40; FD&C YELLOW NO. 6; gelatin; glycerin; polyethylene glycol 400; propylene glycol; sorbitol; titanium dioxide

Colace 50 mg

Drug Facts Colace 100 mg Active ingredient (in each capsule)

Docusate sodium 100 mg

Purpose

Stool softener

Uses

- relieves occasional constipation (irregularity)
- generally produces a bowel movement in 12 to 72 hours

Do not use

- if you are presently taking mineral oil, unless told to do so by a doctor

Ask a doctor before use if you have

- stomach pain
- nausea
- vomiting
- noticed a sudden change in bowel movements that continues over a period of 2 weeks

Stop use and ask a doctor if

- you have rectal bleeding or fail to have a bowel movement after use of a laxative.
  These could be signs of a serious condition.
- you need to use a stool softener laxative for more than 1 week

PREGNANCY OR BREAST FEEDING

If pregnant or breast-feeding, ask a health professional before use.

Keep out of reach of children. In case of overdose, get medical help or contact a Poison Control Center right away.

DOSAGE AND ADMINISTRATION

Directions: Take only by mouth. Doses may be taken as a single daily dose or in divided doses.

adults and children 12 years and over | take 1-3 capsules daily
children 2 to under 12 years of age | take 1 capsule daily
children under 2 years | ask a doctor

Other Information

- each tablet contains: sodium 5 mg
  VERY LOW SODIUM
- store at 25°C (77°F); excursions permitted between 15°-30°C (59°-86°F)

Keep tightly closed.

Inactive ingredients

D&C Red No. 33, FD&C Red No. 40, FD&C Yellow No. 6, gelatin, glycerin, PEG 400, propylene glycol, sorbitol, titanium dioxide

©2009 Purdue Products L.P.

Dist. by: Purdue Products L.P.
Stamford, CT 06901-3431

302112-0B

Additional bar code label applied by:
Physicians Total Care, Inc.
Tulsa, Oklahoma 74146

PACKAGE LABEL

Colace

100mg

NDC 54868-2337-2
30 capsules